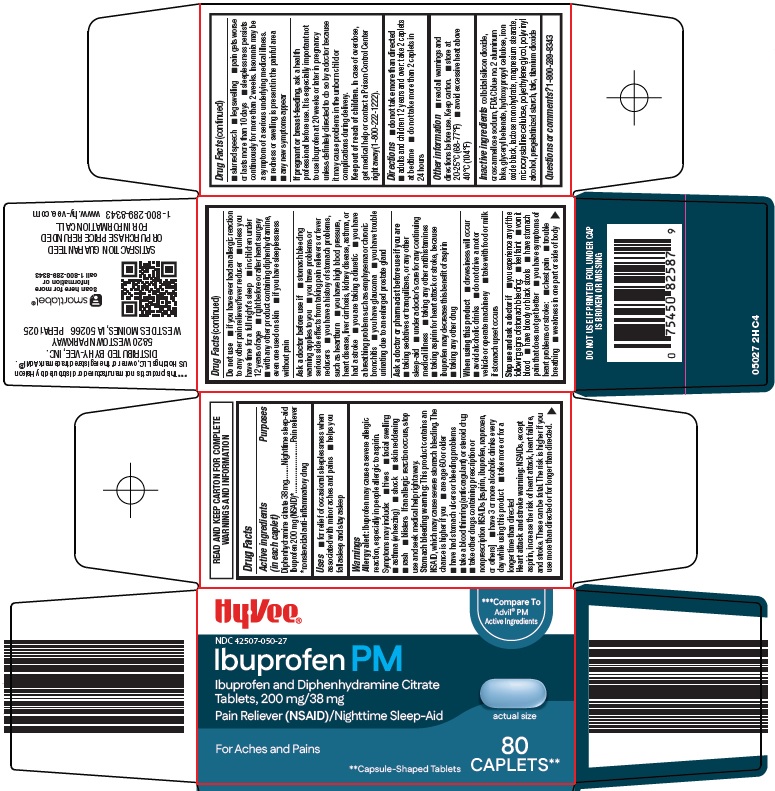 DRUG LABEL: ibuprofen pm
NDC: 42507-050 | Form: TABLET, FILM COATED
Manufacturer: HyVee Inc
Category: otc | Type: HUMAN OTC DRUG LABEL
Date: 20260114

ACTIVE INGREDIENTS: DIPHENHYDRAMINE CITRATE 38 mg/1 1; IBUPROFEN 200 mg/1 1
INACTIVE INGREDIENTS: SILICON DIOXIDE; CROSCARMELLOSE SODIUM; FD&C BLUE NO. 2 ALUMINUM LAKE; GLYCERYL DIBEHENATE; HYDROXYPROPYL CELLULOSE, UNSPECIFIED; FERROSOFERRIC OXIDE; LACTOSE MONOHYDRATE; MAGNESIUM STEARATE; MICROCRYSTALLINE CELLULOSE; POLYETHYLENE GLYCOL, UNSPECIFIED; POLYVINYL ALCOHOL, UNSPECIFIED; TALC; TITANIUM DIOXIDE

Hy-Vee, Inc. Ibuprofen PM Drug Facts

Active ingredients (in each caplet)

Diphenhydramine citrate 38 mg

Ibuprofen 200 mg (NSAID)*

*nonsteroidal anti-inflammatory drug

Purposes

Nighttime sleep-aid

Pain reliever

Uses

1. for relief of occasional sleeplessness when associated with minor aches and pains
2. helps you fall asleep and stay asleep

Warnings

Allergy alert: Ibuprofen may cause a severe allergic reaction, especially in people allergic to aspirin. Symptoms may include:

1. hives
2. facial swelling
3. asthma (wheezing)
4. shock
5. skin reddening
6. rash
7. blisters

If an allergic reaction occurs, stop use and seek medical help right away.

Stomach bleeding warning: This product contains an NSAID, which may cause severe stomach bleeding. The chance is higher if you

1. are age 60 or older
2. have had stomach ulcers or bleeding problems
3. take a blood thinning (anticoagulant) or steroid drug
4. take other drugs containing prescription or nonprescription NSAIDs [aspirin, ibuprofen, naproxen, or others]
5. have 3 or more alcoholic drinks every day while using this product
6. take more or for a longer time than directed

Heart attack and stroke warning: NSAIDs, except aspirin, increase the risk of heart attack, heart failure, and stroke. These can be fatal. The risk is higher if you use more than directed or for longer than directed.

Do not use

1. if you have ever had an allergic reaction to any other pain reliever/fever reducer
2. unless you have time for a full night’s sleep
3. in children under 12 years of age
4. right before or after heart surgery
5. with any other product containing diphenhydramine, even one used on skin
6. if you have sleeplessness without pain

Ask a doctor before use if

1. stomach bleeding warning applies to you
2. you have problems or serious side effects from taking pain relievers or fever reducers
3. you have a history of stomach problems, such as heartburn
4. you have high blood pressure, heart disease, liver cirrhosis, kidney disease, asthma, or had a stroke
5. you are taking a diuretic
6. you have a breathing problem such as emphysema or chronic bronchitis
7. you have glaucoma
8. you have trouble urinating due to an enlarged prostate gland

Ask a doctor or pharmacist before use if you are

1. taking sedatives or tranquilizers, or any other sleep-aid
2. under a doctor’s care for any continuing medical illness
3. taking any other antihistamines
4. taking aspirin for heart attack or stroke, because ibuprofen may decrease this benefit of aspirin
5. taking any other drug

When using this product

1. drowsiness will occur
2. avoid alcoholic drinks
3. do not drive a motor vehicle or operate machinery
4. take with food or milk if stomach upset occurs

Stop use and ask a doctor if

1. you experience any of the following signs of stomach bleeding:
2. feel faint
3. vomit blood
4. have bloody or black stools
5. have stomach pain that does not get better
6. you have symptoms of heart problems or stroke:
7. chest pain
8. trouble breathing
9. weakness in one part or side of body
10. slurred speech
11. leg swelling
12. pain gets worse or lasts more than 10 days
13. sleeplessness persists continuously for more than 2 weeks. Insomnia may be a symptom of a serious underlying medical illness.
14. redness or swelling is present in the painful area
15. any new symptoms appear

If pregnant or breast-feeding,

ask a health professional before use. It is especially important not to use ibuprofen at 20 weeks or later in pregnancy unless definitely directed to do so by a doctor because it may cause problems in the unborn child or complications during delivery.

Keep out of reach of children.

In case of overdose, get medical help or contact a Poison Control Center right away (1-800-222-1222).

Directions

1. do not take more than directed
2. adults and children 12 years and over: take 2 caplets at bedtime
3. do not take more than 2 caplets in 24 hours

Other information

1. read all warnings and directions before use. Keep carton.
2. store at 20-25°C (68 -77°F)
3. avoid excessive heat above 40°C (104°F)

Inactive ingredients

colloidal silicon dioxide, croscarmellose sodium, FD&C blue no. 2 aluminum lake, glyceryl behenate, hydroxypropyl cellulose, iron oxide black, lactose monohydrate, magnesium stearate, microcrystalline cellulose, polyethylene glycol, polyvinyl alcohol, pregelatinized starch, talc, titanium dioxide

Questions or comments?

1-800-289-8343

Principal Display Panel

Hy•Vee®

Compare To Advil® PM Active Ingredients

Ibuprofen PM

Ibuprofen and Diphenhydramine Citrate Tablets, 200 mg/38 mg

Pain Reliever (NSAID)/Nighttime Sleep-Aid

actual size

For Aches and Pains

80 CAPLETS**

**Capsule-Shaped Tablets